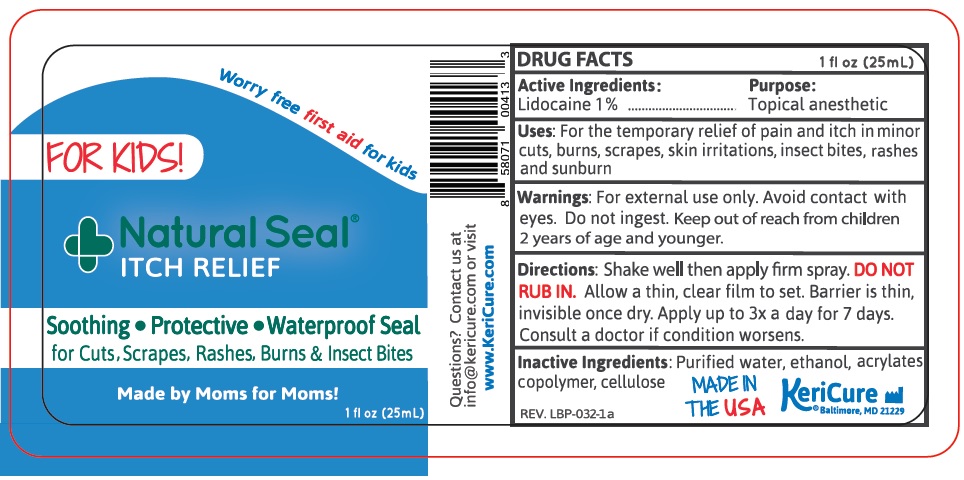 DRUG LABEL: Natural Seal Itch Relief for Kids
NDC: 78280-712 | Form: SPRAY
Manufacturer: Kericure Inc.
Category: otc | Type: HUMAN OTC DRUG LABEL
Date: 20241212

ACTIVE INGREDIENTS: LIDOCAINE 10 mg/1 mL
INACTIVE INGREDIENTS: WATER; ALCOHOL; BUTYL ACRYLATE/METHYL METHACRYLATE/METHACRYLIC ACID COPOLYMER (18000 MW); HYDROXYETHYL CELLULOSE (2000 MPA.S AT 1%)

Natural Seal® ITCH RELIEF

Active Ingredients:

Lidocaine 1%

Purpose:

Topical anesthetic

Uses:

For the temporary relief of pain and itch in minor cuts, burns, scrapes, skin irritations, insect bites, rashes and sunburn

Warnings:

For external use only. Avoid contact with eyes. Do not ingest.

KEEP OUT OF REACH OF CHILDREN

Keep out of reach from children 2 years of age and younger.

Directions:

Shake well then apply firm spray. DO NOT RUB IN. Allow a thin, clear film to set. Barrier is thin, invisible once dry. Apply up to 3× a day for 7 days. Consult a doctor if condition worsens.

Inactive Ingredients:

Purified water, ethanol, acrylates copolymer, cellulose

FOR KIDS!

Worry free first aid for kids

Soothing • Protective • Waterproof Seal

for Cuts, Scrapes, Rashes, Burns & Insect Bites

Made by Moms for Moms!

Questions? Contact us at info@kericure.com or visit www.KeriCure.com

MADE IN THE USA

KeriCure®

Baltimore, MD 21229